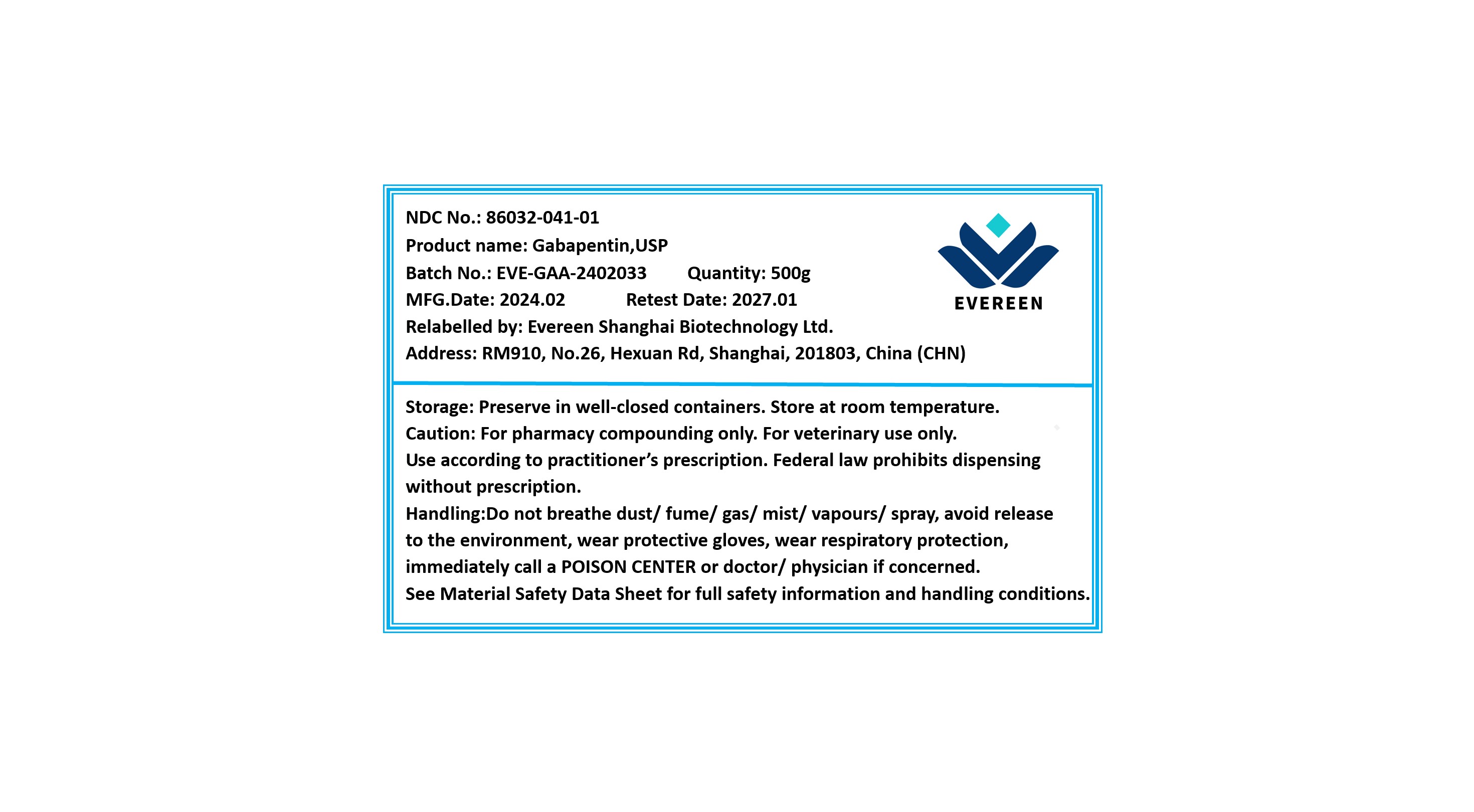 DRUG LABEL: Gabapentin
NDC: 86032-041 | Form: POWDER
Manufacturer: Evereen Shanghai Biotechnology Ltd.
Category: other | Type: BULK INGREDIENT - ANIMAL DRUG
Date: 20250106

ACTIVE INGREDIENTS: GABAPENTIN 1 g/1 g

Gabapentin